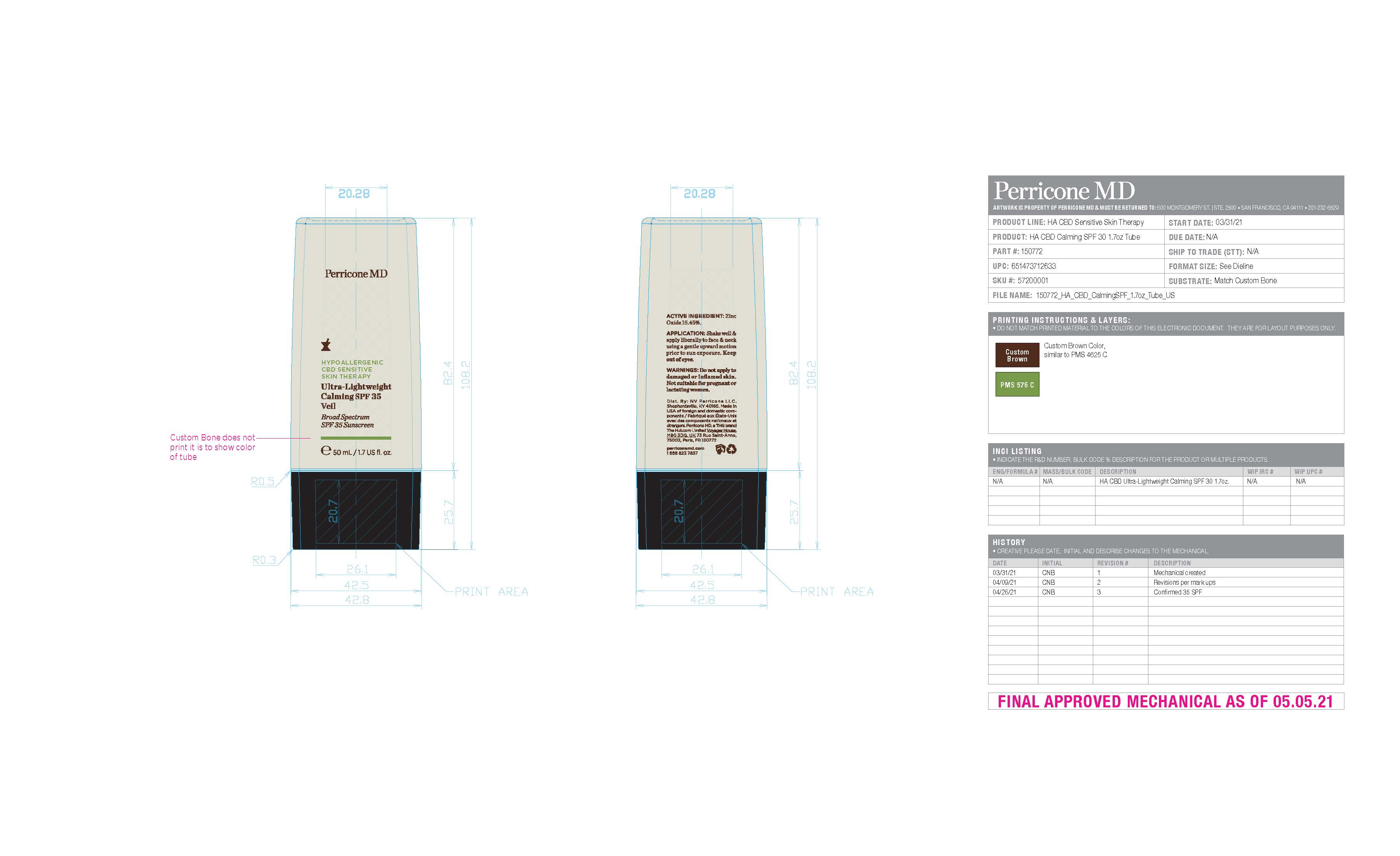 DRUG LABEL: HYPOALLERGENIC CBD SENSITIVE SKIN THERAPY Ultra-Lightweight Calming Veil SPF 35
NDC: 45634-715 | Form: CREAM
Manufacturer: NV Perricone LLC
Category: otc | Type: HUMAN OTC DRUG LABEL
Date: 20230907

ACTIVE INGREDIENTS: ZINC OXIDE 7.725 mg/50 mg
INACTIVE INGREDIENTS: LEVOMENOL; OCTYLDODECANOL; WATER; POLYHYDROXYSTEARIC ACID (2300 MW); ISODODECANE; BUTYLOCTYL SALICYLATE; GLYCERIN; PROPANEDIOL; SODIUM CHLORIDE; HYDROXYACETOPHENONE; PROPYLENE CARBONATE; POTASSIUM SORBATE; CANNABIDIOL; XANTHAN GUM; ROSEMARY; ANHYDROUS CITRIC ACID; HELIANTHUS ANNUUS FLOWERING TOP; TOCOPHEROL; ALKYL (C12-15) BENZOATE; CANNABIS SATIVA SEED OIL; COCO-CAPRYLATE/CAPRATE; BUTYL ACRYLATE/METHYL METHACRYLATE/METHACRYLIC ACID COPOLYMER (18000 MW); STEAROYL GLUTAMIC ACID; SODIUM BENZOATE; RICE BRAN; POLYGLYCERYL-4 DIISOSTEARATE/POLYHYDROXYSTEARATE/SEBACATE; STEARALKONIUM HECTORITE; CASTOR OIL; CALCIUM GLUCONATE; MEDIUM-CHAIN TRIGLYCERIDES; TRIHEPTANOIN; LINGONBERRY; DILINOLEIC ACID/BUTANEDIOL COPOLYMER; GLYCYRRHIZINATE DIPOTASSIUM; C9-12 ALKANE; GLUCONOLACTONE; CALENDULA OFFICINALIS FLOWER

RECENT MAJOR CHANGES

X